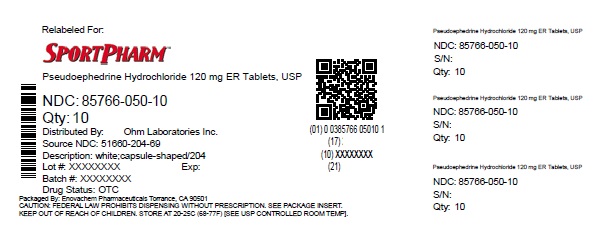 DRUG LABEL: Pseudoephedrine hydrochloride
NDC: 85766-050 | Form: TABLET, FILM COATED
Manufacturer: Sportpharm LLC
Category: otc | Type: HUMAN OTC DRUG LABEL
Date: 20260206

ACTIVE INGREDIENTS: PSEUDOEPHEDRINE HYDROCHLORIDE 120 mg/1 1
INACTIVE INGREDIENTS: CASTOR OIL; SILICON DIOXIDE; HYPROMELLOSE, UNSPECIFIED; MAGNESIUM STEARATE; MICROCRYSTALLINE CELLULOSE; TITANIUM DIOXIDE

Pseudoephedrine hydrochloride

Drug Facts

Active ingredient (in each tablet)

Pseudoephedrine HCl, USP 120 mg

Purpose

Nasal decongestant

Uses

- temporarily relieves nasal congestion due to the common cold, hay fever or other upper respiratory allergies
- temporarily relieves sinus congestion and pressure

Warnings

DO NOT USE

Do not useif you are now taking a prescription monoamine oxidase inhibitor (MAOI) (certain drugs for depression, psychiatric or emotional conditions, or Parkinson's disease), or for 2 weeks after stopping the MAOI drug. If you do not know if your prescription drug contains an MAOI, ask a doctor or pharmacist before taking this product.

Ask a doctor before use if you have

- heart disease
- high blood pressure
- thyroid disease
- diabetes
- trouble urinating due to an enlarged prostate gland

When using this product do not exceed recommended dosage

Stop use and ask a doctor if

- nervousness, dizziness, or sleeplessness occur
- symptoms do not improve within 7 days or occur with a fever

PREGNANCY OR BREAST FEEDING

If pregnant or breast-feeding,ask a health professional before use.

Keep out of reach of children.In case of overdose, get medical help or contact a Poison Control Center right away. (1-800-222-1222)

Directions

adults and children 12 years and over | - take 1 tablet every 12 hours - do not take more than 2 tablets in 24 hours
children under 12 years | do not use this product in children under 12 years of age

Other information

- store at 59° to 77° F in a dry place. Protect from light
- TAMPER EVIDENT: DO NOT USE IF BLISTER UNITS ARE TORN, BROKEN OR SHOW ANY SIGNS OF TAMPERING.

Inactive ingredients

castor oil, colloidal silicon dioxide, hypromellose, magnesium stearate, microcrystalline cellulose, titanium dioxide

Questions?

call 1-800-406-7984